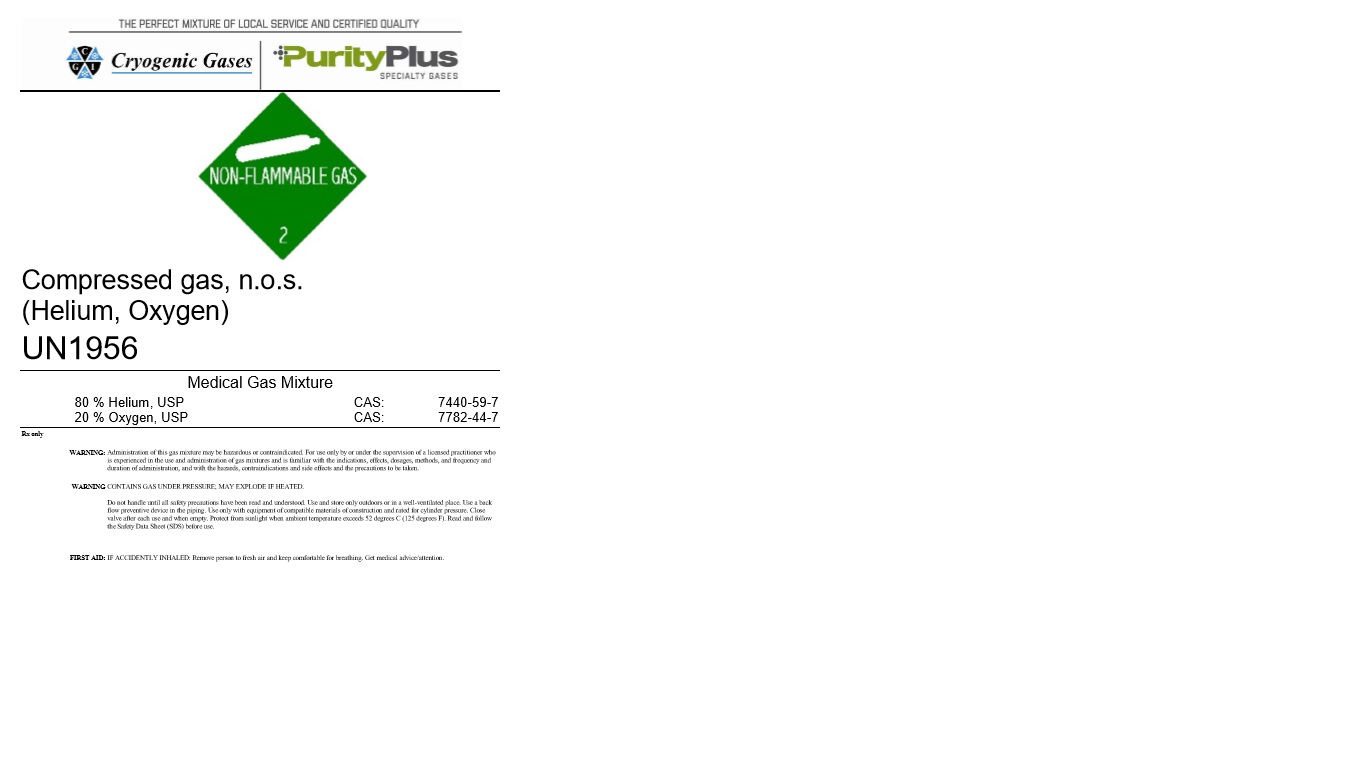 DRUG LABEL: Heliox
NDC: 62273-007 | Form: GAS
Manufacturer: Metro Welding Supply Corporation
Category: prescription | Type: HUMAN PRESCRIPTION DRUG LABEL
Date: 20251020

ACTIVE INGREDIENTS: OXYGEN 200 mL/1 L
INACTIVE INGREDIENTS: HELIUM 800 mL/1 L

Heliox 20/80

PACKAGE LABEL

THE PERFECT MIXTURE OF LOCAL SERVICE AND CERTIFIED QUALITY

Cryogenic Gases

PurityPlus SPECIALTY GASES

Compressed gas, n.o.s. (Helium, Oxygen)

UN1956

Medical Gas Mixture

80 % Helium, USP CAS: 7440-59-7

20 % Oxygen, USP CAS: 7782-44-7

Rx only:

WARNING: Administration of this gas mixture may be hazardous or contraindicated. For use only by or under the supervision of a licensed practitioner who is experienced in the use and administration of gas mixtures and is familiar with the indications, effects, dosages, methods, and frequency and duration of administration, and with the hazards, contraindications and side effects and the precautions to be taken.

WARNING CONTAINS GAS UNDER PRESSURE; MAY EXPLODE IF HEATED.

Do not handle until all safety precautions have been read and understood. Use and store only outdoors or in a well-ventilated place. Use a back flow preventive device in the piping. Use only with equipment of compatible materials of construction and rated for cylinder pressure. Close valve after each use and when empty. Protect from sunlight when ambient temperature exceeds 52 degrees C (125 degrees F). Read and follow the Safety Data Sheet (SDS) before use.

FIRST AID: IF ACCIDENTLY INHALED: Remove person to fresh air and keep comfortable for breathing. Get medical advice/attention.

DO NOT REMOVE THIS PRODUCT LABEL

For Medical Use Only.

Ver. 3.90

Volume: 205CF

Cryogenic Gases

12620 Southfield Fwy.

Detroit, MI, 48223

313-834-1660